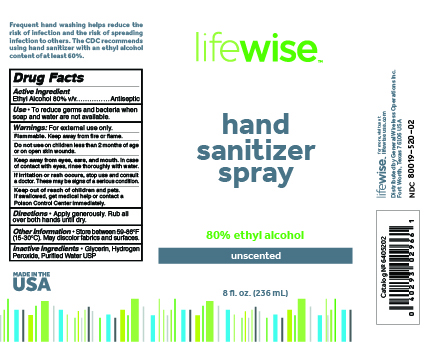 DRUG LABEL: LIFEWISE HAND SANITIZER
NDC: 80019-520 | Form: SPRAY
Manufacturer: General Wireless Operations Inc.
Category: otc | Type: HUMAN OTC DRUG LABEL
Date: 20201029

ACTIVE INGREDIENTS: ALCOHOL 80 mL/100 mL
INACTIVE INGREDIENTS: GLYCERIN 1.45 mL/100 mL; HYDROGEN PEROXIDE 0.125 mL/100 mL; WATER

LIFEWISE HAND SANITIZER

This is a hand sanitizer manufactured according to the Temporary Policy for Preparation of Certain Alcohol-Based Hand Sanitizer Products During the Public Health Emergency (CoViD-19); Guidance for Industry.

The hand sanitizer is manufactured using only the following United States Pharmacopoeia (USP) grade ingredients in the preparation of the product (percentage in final product formulation) consistent with World Health Organization (WHO) recommendations:

1. Alcohol (ethanol) (USP or Food Chemical Codex (FCC) grade) (80%, volume/volume (v/v)) in an aqueous solution denatured according to Alcohol and Tobacco Tax and Trade Bureau regulations in 27 CFR part 20.
2. Glycerol (1.45% v/v).
3. Hydrogen peroxide (0.125% v/v).
4. Sterile distilled water or boiled cold water.

The firm does not add other active or inactive ingredients. Different or additional ingredients may impact the quality and potency of the product.

Active Ingredient(s)

Ethyl Alcohol 80% v/v. Purpose: Antiseptic

Purpose

Antiseptic, Hand Sanitizer

Use

To reduce germs and bacteria when soap and water are not available.

Warnings

For external use only. Flammable. Keep away from fire or flame.

Do not use on children less than 2 months of age or on open skin wounds.

WHEN USING

Keep away from eyes, ears, and mouth. In case of contact with eyes, rinse thoroughly with water.

STOP USE

If irritation or rash occurs, stop use and consult a doctor. These may be signs of a serious condition.

Keep out of reach of children and pets. If swallowed, get medical help or contact a Poison Control Center immediately.

Directions

Apply generously. Rub all over both hands until dry.

Other information

Store between 59-86°F (15-30°C). May discolor fabrics and surfaces.

Inactive ingredients

glycerin, hydrogen peroxide, purified water USP

RECENT MAJOR CHANGES

- Update and clarify use cases, warnings, and directions of use. (8/27/2020)
- Update label design. Added link to lifewiseusa.com. Clarified Drug Information panel. (10/29/2020)

Package Label - Principal Display Panel

NDC: 80019-520-01/02/03

Catalog No. 6405201/2/3